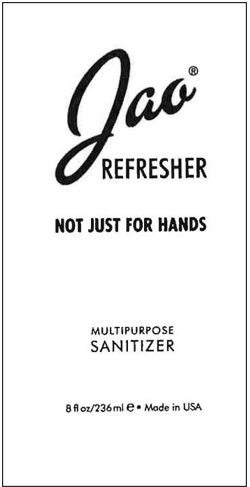 DRUG LABEL: Refresher
NDC: 69662-111 | Form: LIQUID
Manufacturer: Jao Limited
Category: otc | Type: HUMAN OTC DRUG LABEL
Date: 20250613

ACTIVE INGREDIENTS: ALCOHOL 65 mL/100 mL
INACTIVE INGREDIENTS: ALOE VERA LEAF; GLYCERIN; PANTHENOL; ALLYL METHACRYLATE/GLYCOL DIMETHACRYLATE CROSSPOLYMER (LOW ALLYL METHACRYLATE); AMINOMETHYLPROPANOL; CHAMOMILE; CALENDULA ARVENSIS LEAF; ACETYLATED SUCROSE DISTEARATE; LAVENDER OIL; EUCALYPTUS OIL; WATER; GERANIUM OIL, ALGERIAN TYPE; SAGE OIL; GREEN TEA LEAF; POLYSORBATE 20

JAO Refresher

Active Ingredient

Ethyl Alcohol 65%

Purpose

Antimicrobial

Uses:

Sanitizer to help reduce bacteria on skin.
For use when water is not available.

Warnings

For external use only. Flammable.
Keep away from heat or flame.

When using this product

- Keep out of eyes. In case of contact, flush thoroughly with water.
- Avoid contact with broken skin.

Stop and ask a doctor

if irritation develops.

Keep out of reach of children.

If swallowed get medical help or contact Poison Control Center right away.

Directions

Apply on hands, rub briskly until dry.

Other Info

- Do not store above 100oF (43oC).
- May discolor certain fabrics or surfaces.

Inactive Ingredients

Acrylates/C10-30 Alkyl Acrylate Crosspolymer, Aloe Barbadensis, Amino-Methyl Propanol, Calendula Extract, Chamomile Extract, dl-Panthenol, Essential Oils (Lavender, Tea Tree, Eucalyptus, Geranium, Clary Sage), Glycerine and Glyceryl Polyacrylate, PPG-20 Methyl Glucose Ether Distearate, Water

PRINCIPAL DISPLAY PANEL

JAO®
REFRESHER
NOT JUST FOR HANDS

MULTIPURPOSE
SANITIZER

8 fl oz/236 ml ℮ ∙ Made in USA

Distributed by JAO Ltd Lansdale, PA 19446
©JAO Ltd 888 296 8685 MADE IN USE
WWW.JAOBRAND.COM

Label